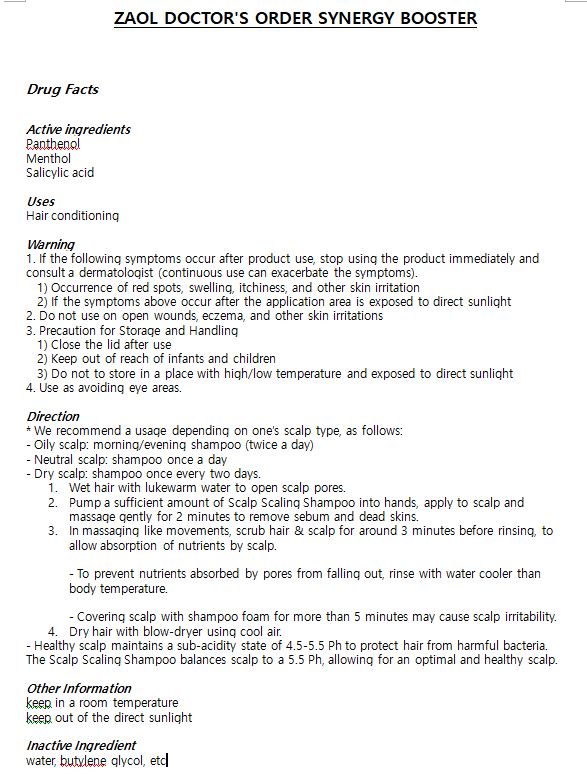 DRUG LABEL: ZAOL DOCTORS ORDER SYNERGY BOOSTER
NDC: 71175-0004 | Form: LIQUID
Manufacturer: zaol
Category: otc | Type: HUMAN OTC DRUG LABEL
Date: 20180607

ACTIVE INGREDIENTS: SALICYLIC ACID 0.25 g/100 mL; PANTHENOL 0.2 g/100 mL; MENTHOL 0.3 g/100 mL
INACTIVE INGREDIENTS: BUTYLENE GLYCOL; WATER

ACTIVE INGREDIENT

Panthenol, Salicylic Acid, Menthol

INACTIVE INGREDIENT

Water, Glycerin, Butylene Glycol, etc.

PURPOSE

Hair conditioning

Keep out of reach of the children

WARNINGS

1. If the following symptoms occur after product use, stop using the product immediately and consult a dermatologist (continuous use can exacerbate the symptoms).
1) Occurrence of red spots, swelling, itchiness, and other skin irritation
2) If the symptoms above occur after the application area is exposed to direct sunlight

2. Do not use on open wounds, eczema, and other skin irritations

3. Precaution for Storage and Handling
1) Close the lid after use
2) Keep out of reach of infants and children
3) Do not to store in a place with high/low temperature and exposed to direct sunlight

4. Use as avoiding eye areas.

INDICATIONS AND USAGE

1. Wash hair with the Scalp Scaling Shampoo and dry thoroughly.
  - Use blow-dryer’s cool air function to dry hair
2. On a dry scalp, apply the Synergy Booster by tapping gently on the area (15 to 20 times).
  - The Synergy Booster being sprayed directly from the container nozzles, its scalp penetrability is very high and, combined with scalp stimulation through massaging and blood circulation activation, absorption rates get higher.
3. Tap and press on the scalp using finger.
  - After using Synergy Booster, make sure that all the topical solution is absorbed by gently tapping on the scalp.

DOSAGE AND ADMINISTRATION

For external use only